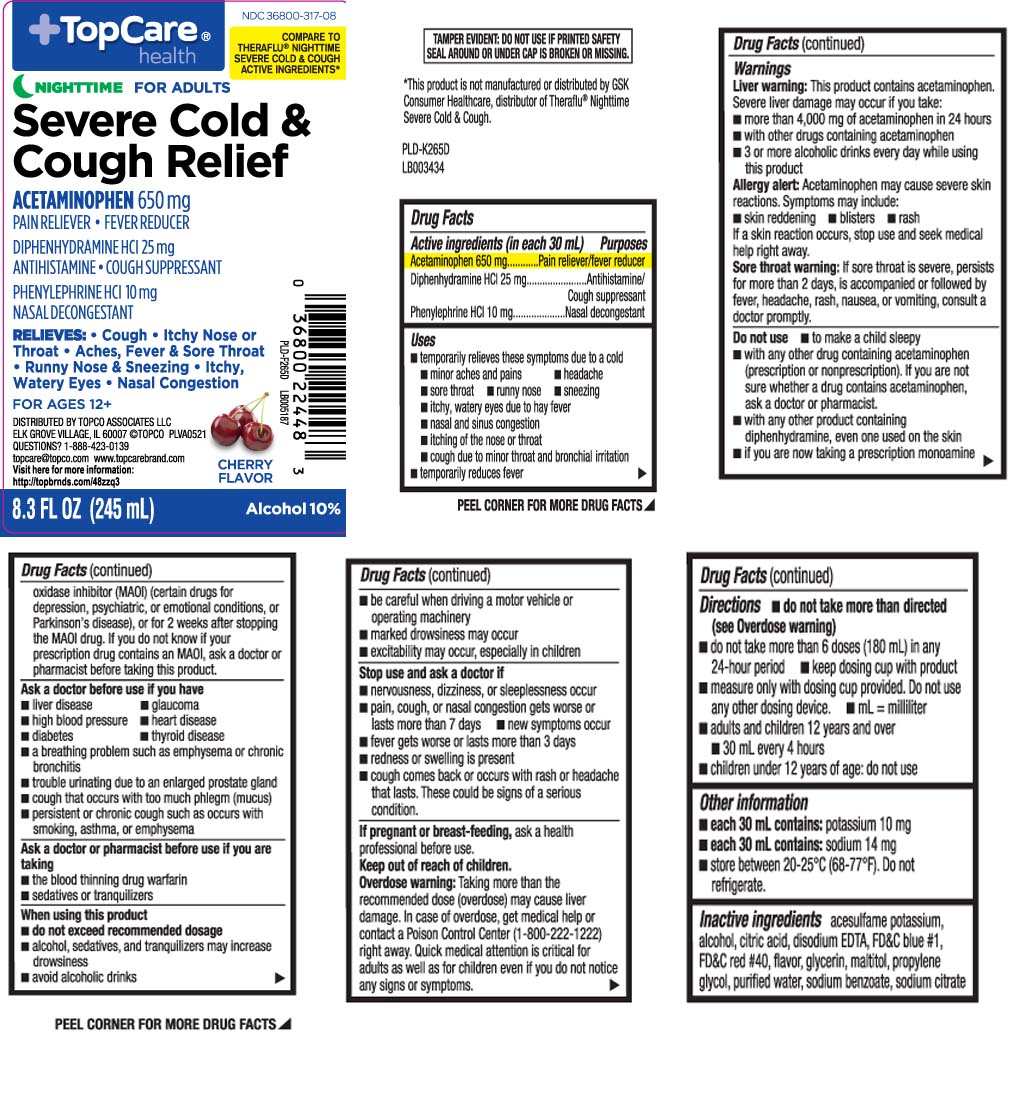 DRUG LABEL: Flu Relief Therapy
NDC: 36800-317 | Form: LIQUID
Manufacturer: TOP CARE (Topco Associates LLC)
Category: otc | Type: HUMAN OTC DRUG LABEL
Date: 20231013

ACTIVE INGREDIENTS: ACETAMINOPHEN 650 mg/30 mL; DIPHENHYDRAMINE HYDROCHLORIDE 25 mg/30 mL; PHENYLEPHRINE HYDROCHLORIDE 10 mg/30 mL
INACTIVE INGREDIENTS: ACESULFAME POTASSIUM; ALCOHOL; ANHYDROUS CITRIC ACID; EDETATE DISODIUM; FD&C BLUE NO. 1; FD&C RED NO. 40; GLYCERIN; MALTITOL; PROPYLENE GLYCOL; WATER; SODIUM BENZOATE; TRISODIUM CITRATE DIHYDRATE

Drug Facts

Active ingredients (in each 30 mL)

Acetaminophen 650 mg

Diphenhydramine HCl 25 mg

Phenylephrine HCl 10 mg

Purposes

Pain reliever/fever reducer

Antihistamine/Cough suppressant

Nasal decongestant

Uses

- temporarily relieves these symptoms due to a cold
  - minor aches and pains
  - headache
  - sore throat
  - runny nose
  - itchy, watery eyes
  - sneezing
  - nasal and sinus congestion
  - itching of the nose or throat
  - cough due to minor throat and bronchial irritation
- temporarily reduces fever

Warnings

Liver warnings: This product contains acetaminophen. Severe liver damage may occur if you take:

- more than 4,000 mg of acetaminophen in 24 hours
- with other drugs containing acetaminophen
- 3 or more alcoholic drinks every day while using this product

Allergy alert: Acetaminophen may cause severe skin reactions. symptoms may include:

- skin reddening
- blisters
- rash

If a skin reaction occurs, stop use and seek medical help right away.

Sore throat warning: If sore throat is severe, persists for more than 2 days, is accompanied or followed by fever, headache, rash, nausea, or vomiting, consult a doctor promptly.

Do not use

- to make a child sleepy
- if you are now taking a prescription monoamine oxidase inhibitor (MAOI) (certain drugs for depression, psychiatric or emotional conditions, or Parkinson’s disease), or for 2 weeks after stopping the MAOI drug. If you do not know if your prescription drug contains an MAOI, ask a doctor or pharmacist before taking this product.
- with any other product containing diphenhydramine, even one used on skin
- with any other drug containing acetaminophen (prescription or non-prescription). If you are not sure whether a drug contains acetaminophen, ask a doctor or pharmacist.

Ask a doctor before use if you have

- liver disease
- glaucoma
- heart disease
- thyroid disease
- high blood pressure
- diabetes
- a breathing problem such as emphysema or chronic bronchitis
- trouble urinating due to an enlarged prostate gland
- cough that occurs with too much phlegm (mucus)
- persistent or chronic cough such as occurs with smoking, asthma, or emphysema

Ask a doctor or pharmacist before use if you are taking

- the blood thinning drug warfarin
- sedatives or tranquilizers

When using this product

- do not exceed recommended dosage
- alcohol, sedatives, and tranquilizers may increase drowsiness
- avoid alcoholic drinks
- be careful when driving a motor vehicle or operating machinery
- marked drowsiness may occur
- excitability may occur, especially in children

Stop use and ask a doctor if

- nervousness, dizziness, or sleeplessness occurs
- pain, cough or nasal congestion gets worse or lasts more than 7 days
- new symptoms occur
- fever gets worse or lasts more than 3 days
- redness or swelling is present
- cough comes back or occurs with a rash or headache that lasts

These could be signs of a serious condition.

If pregnant or breast-feeding,

ask a health professional before use.

Keep out of reach of children.

Overdose warning: Taking more than the recommended dose (overdose) may cause liver damage. In case of overdose, get medical help or contact a Poison Control Center (1-800-222-1222) right away. Quick medical attention is critical for adults as well as for children even if you do not notice any signs or symptoms.

Directions

- do not take more than directed (see overdose warning)
- do not take more than 6 doses in any 24-hour period
- measure only with dosing cup provided. Do not use any other dosing device
- mL=milliliter
- keep dosing cup with product
- adults and children 12 years and over
  - 30 mL every 4 hours
- children under 12 years of age; do not use

Other information

- each 30 mL contains: potassium 10 mg
- each 30 mL contains: sodium 14 mg
- store between 20-25ºC (68-77ºF). Do not refrigerate.

Inactive ingredients

acesulfame potassium, alcohol, citric acid, edetate disodium, FD&C blue #1, FD&C red #40, flavors, glycerin, maltitol, propylene glycol, purified water, sodium benzoate, sodium citrate

Principal Display Panel

COMPARE TO THERAFLU® NIGHTTIME SEVERE COLD & COUGH ACTIVE INGREDIENTS*

NIGHTTIME FOR ADULTS

Severe Cold & Cough Relief

ACETAMINOPHEN 650 mg PAIN RELIEVER • FEVER REDUCER

DIPHENHYDRAMINE HCl 25 mg ANTIHISTAMINE • COUGH SUPPRESSANT

PHENYLEPHRINE HCl 10 mg NASAL DECONGESTANT

RELIEVES:

- Cough
- Itchy Bose or Throat
- Aches, Fever & Sore Throat
- Runny Nose & Sneezing
- Itchy, Watery Eyes
- Nasal Congestion

FOR AGES 12 +

Alcohol 10 %

CHERRY FLAVOR

FL OZ (mL)

*This product is not manufactured or distributed by GSK Consumer Healthcare, Inc., Distributor of Theraflu® Nighttime Severe Cold & Cough.

TAMPER EVIDENT: DO NOT USE IF PRINTED SAFETY SEAL AROUND OR UNDER CAP IS BROKEN OR MISSING

DISTRIBUTED BY TOPCO ASSOCIATES LLC

ELK GROVE VILLAGE, IL 60007©TOPCO

QUESTIONS? 1-888-423-0139

topcare@topcare.comwww.topcarebrand.com

Product Label

TOPCARE HEALTH Severe Cold & Cough Relief